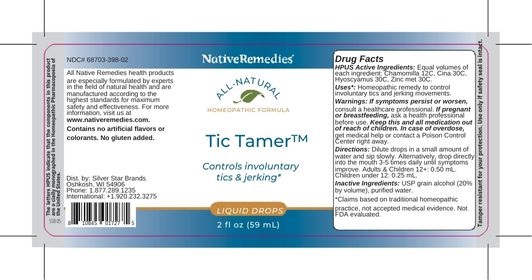 DRUG LABEL: NativeRemedies Tic Tamer
NDC: 68703-398 | Form: LIQUID
Manufacturer: Silver Star Brands
Category: homeopathic | Type: HUMAN OTC DRUG LABEL
Date: 20250101

ACTIVE INGREDIENTS: MATRICARIA RECUTITA 12 [hp_C]/59 mL; ARTEMISIA CINA FLOWER 30 [hp_C]/59 mL; ZINC 30 [hp_C]/59 mL; HYOSCYAMUS NIGER 30 [hp_C]/59 mL
INACTIVE INGREDIENTS: ALCOHOL; WATER

NativeRemedies® Tic Tamer™

HPUS Active Ingredient

HPUS Active Ingredients: Equal volumes of each ingredient: Chamomilla 12C, Cina 30C, Hyoscyamus 30C, Zinc met 30C.

The letters HPUS indicate that the components in this product are offically monographed in the Homeopathic Pharmacopoeia of the United States.

Uses*

Uses*: Homeopathic remedy to control involuntary tics and jerking movements.

*Claims based on traditional homeopathic practice, not accepted medical evidence. Not FDA evaluated.

Warnings

Warnings: If symptoms persist or worsen, consult a healthcare professional. If pregnant or breastfeeding, ask a health professional before use. Keep this and all medication out of reach of children. In case of overdose, get medical help or contact a Poison Control Center right away.

Directions

Directions: Dilute drops in a small amount of water and sip slowly. Alternatively, drop directly into the mouth 3-5 times daily until symptoms improve. Adults & Children 12+: 0.50 mL. Children under 12: 0.25 mL.

OTHER SAFETY INFORMATION

Contains no artificial flavors or colorants. No gluten added.

Tamper resistant for your protection. Use only if safety seal is intact.

Inactive Ingredients

Inactive Ingredients: USP grain alcohol (20% by volume), purified water.

KEEP OUT OF REACH OF CHILDREN

Keep this and all medication out of reach of children.

PREGNANCY OR BREAST FEEDING

If pregnant or breastfeeding, ask a health professional before use.

PURPOSE

Controls involuntary tics & jerking.